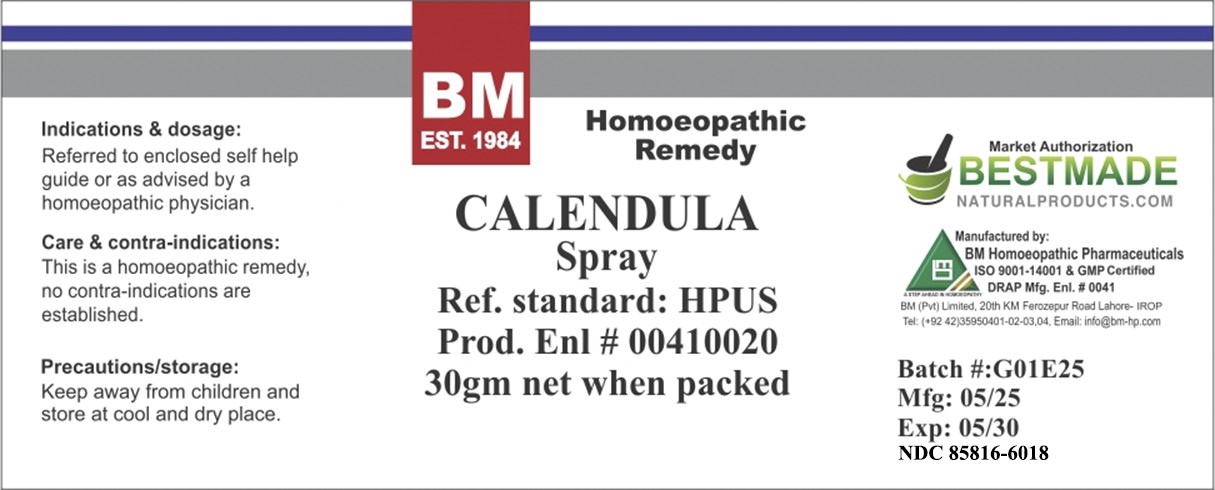 DRUG LABEL: BM Calendula Officinalis
NDC: 85816-6018 | Form: SPRAY
Manufacturer: BM Private Limited
Category: homeopathic | Type: HUMAN OTC DRUG LABEL
Date: 20250627

ACTIVE INGREDIENTS: CALENDULA OFFICINALIS FLOWERING TOP 1 [hp_X]/1 mL
INACTIVE INGREDIENTS: WATER 0.527 mL/1 mL; ALCOHOL 0.473 mL/1 mL

BM Calendula Officinalis Spray

ACTIVE INGREDIENT

calendula officinalis

INACTIVE INGREDIENT

purified water and alcohol

Indications & dosage:
Referred to enclosed self help guide or as advised by a homoeopathic physician.

Indications & dosage:
Referred to enclosed self help guide or as advised by a homoeopathic physician.

PURPOSE

Indications & dosage:
Referred to enclosed self help guide or as advised by a homoeopathic physician.

CONTRAINDICATIONS

Care & contra-indications:
This is a homoeopathic remedy, no contra-indications are established.

WARNINGS

Precautions/storage:
Keep away from children and store at cool and dry place.

KEEP OUT OF REACH OF CHILDREN

Precautions/storage:
Keep away from children and store at cool and dry place.

Entire package label